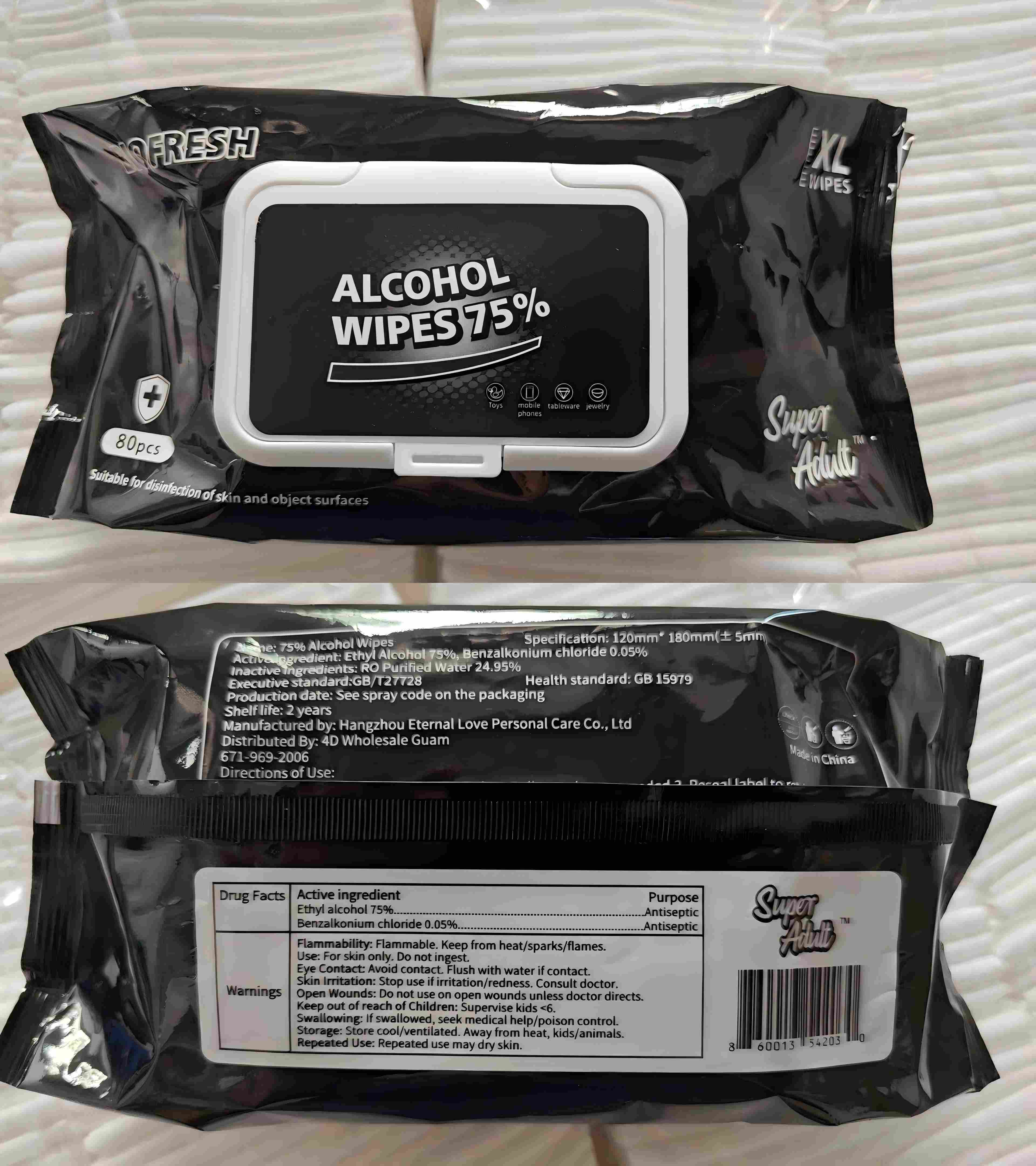 DRUG LABEL: 75% Alcohol Wipes
NDC: 87065-101 | Form: LIQUID
Manufacturer: Hangzhou Eternal Love Personal Care Co., Ltd
Category: otc | Type: HUMAN OTC DRUG LABEL
Date: 20250829

ACTIVE INGREDIENTS: BENZALKONIUM CHLORIDE 0.05 g/100 g; ALCOHOL 75 g/100 g
INACTIVE INGREDIENTS: WATER

Purpose: Antiseptic

ACTIVE INGREDIENT

Active ingredients: Ethyl alcohol 75%; Benzalkonium Chloride 0.05%

INDICATIONS AND USAGE

Use: For skin only. Do not ingest.

Warnings:

Flammability: Flammable. Keep from heat/sparks/flames.

Eye Contact: Avoid contact. Flush with water if contact.

Skin Irritation: Stop use if irritation/redness. Consult doctor.

Open Wounds: Do not use on open wounds unless doctor directs.

Swallowing: If swallowed, seek medical help/poison control.

Storage: Store cool/ventilated. Away from heat, kids/animals.

Repeated Use: Repeated use may dry skin.

DOSAGE AND ADMINISTRATION

Directions of Use:

Open the lid and slowly peel back label.2. Pull out wipes as needed.3. Reseal label to retain moisture.

Keep out of reach of Children: Supervise kids <6.

Inactive ingredients: RO pure water

Label